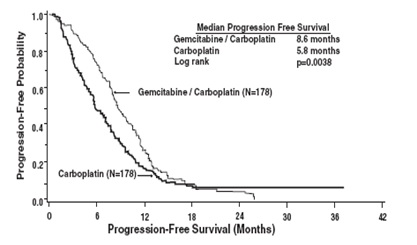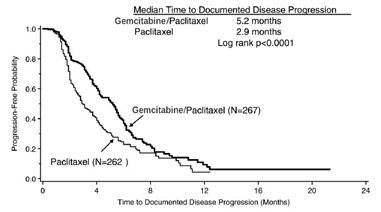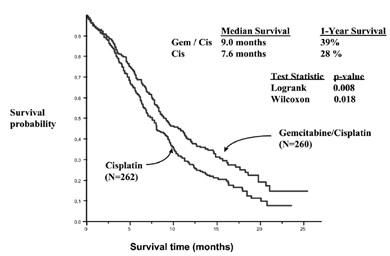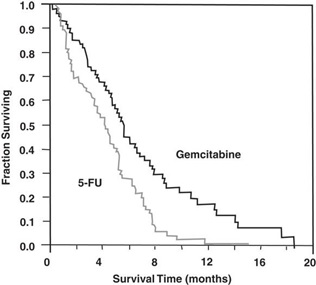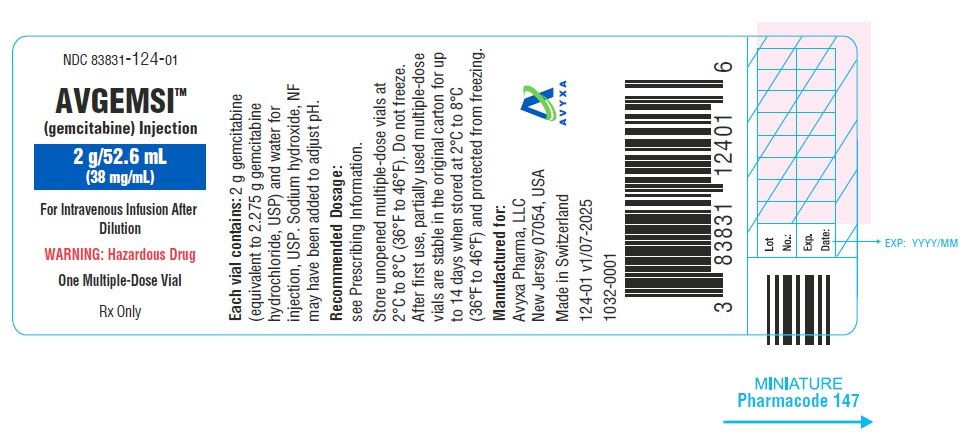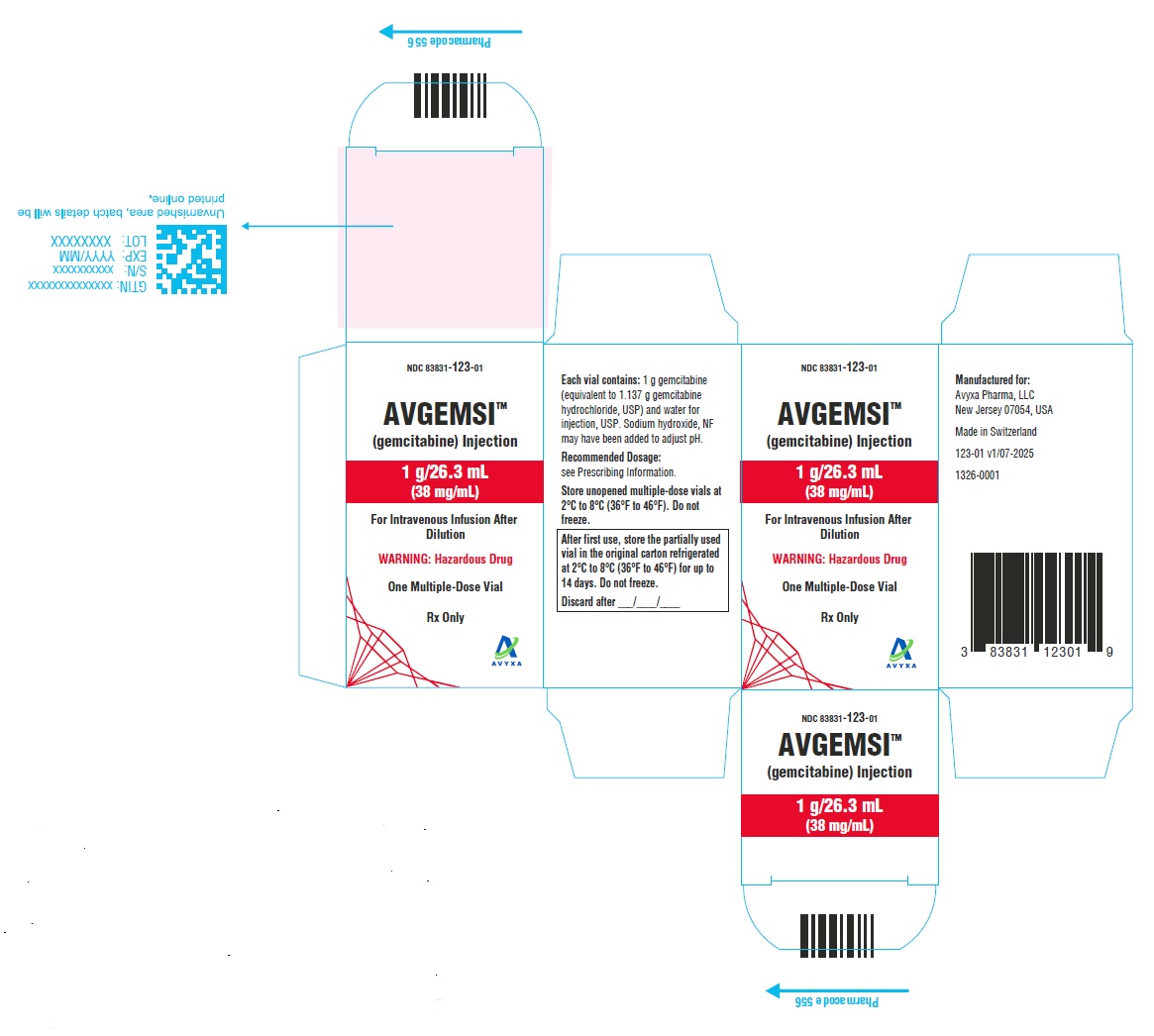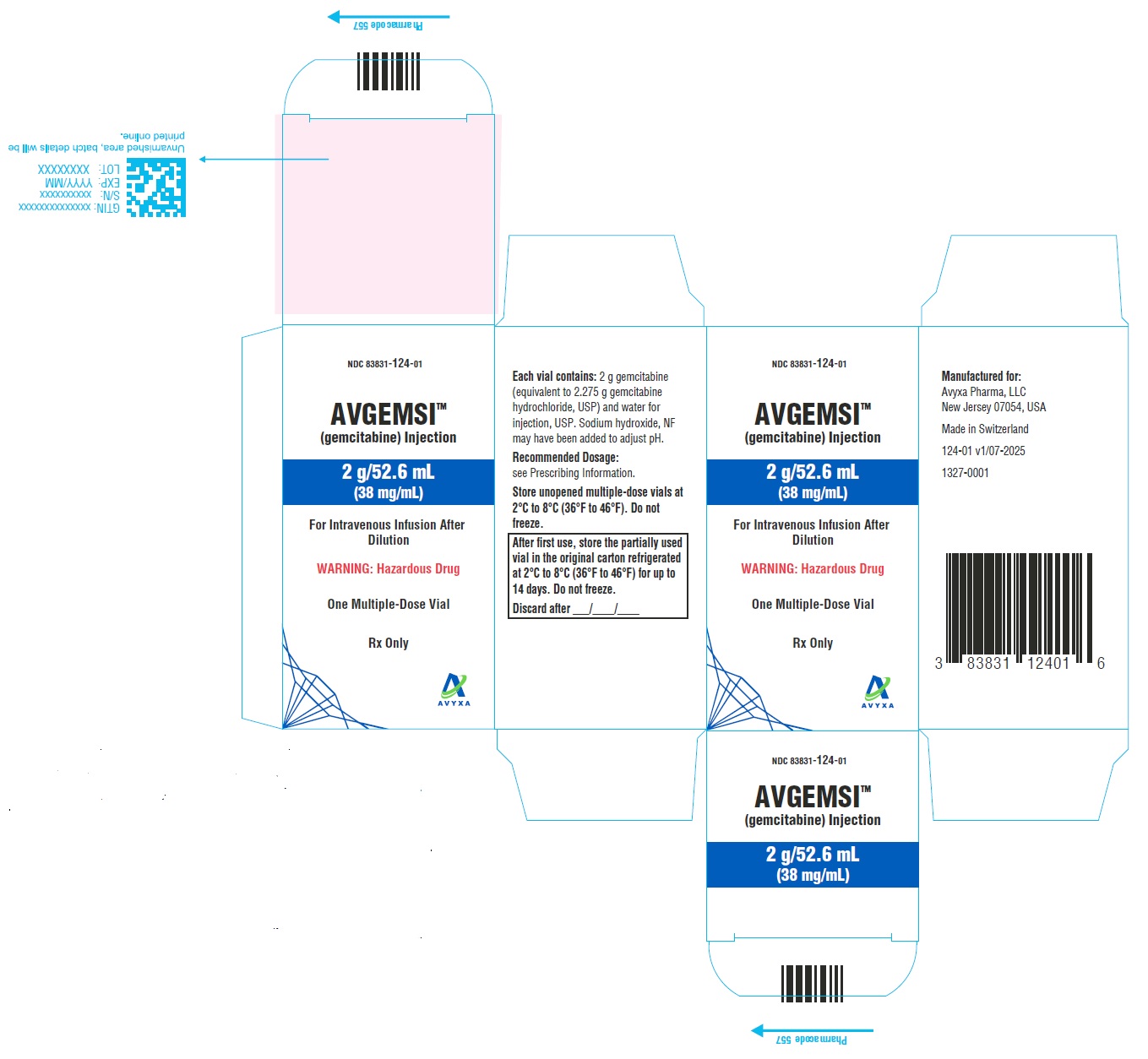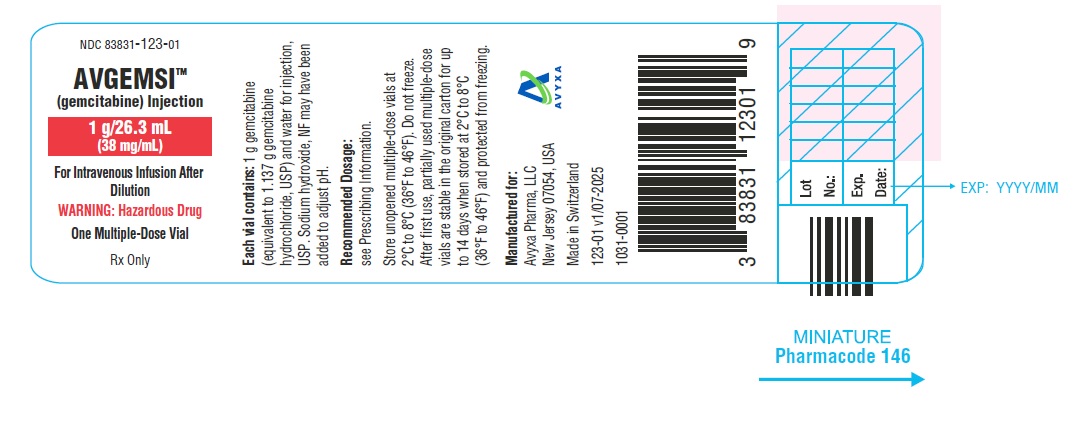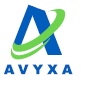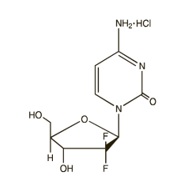 DRUG LABEL: AVGEMSI
NDC: 83831-122 | Form: INJECTION, SOLUTION
Manufacturer: Avyxa Pharma, LLC
Category: prescription | Type: HUMAN PRESCRIPTION DRUG LABEL
Date: 20250804

ACTIVE INGREDIENTS: GEMCITABINE HYDROCHLORIDE 38 mg/1 mL
INACTIVE INGREDIENTS: SODIUM HYDROXIDE; WATER

HIGHLIGHTS OF PRESCRIBING INFORMATION

These highlights do not include all the information needed to use AVGEMSI safely and effectively. See full prescribing information for AVGEMSI.
AVGEMSITM (gemcitabine) injection, for intravenous use
Initial U.S. Approval: 1996

1 INDICATIONS AND USAGE

AVGEMSI is a nucleoside metabolic inhibitor indicated:

- in combination with carboplatin, for the treatment of advanced ovarian cancer that has relapsed at least 6 months after completion of platinum-based therapy. (1.1)
- in combination with paclitaxel, for first-line treatment of metastatic breast cancer after failure of prior anthracycline-containing adjuvant chemotherapy, unless anthracyclines were clinically contraindicated. (1.2)
- in combination with cisplatin, for the treatment of non-small cell lung cancer. (1.3)
- as a single agent for the treatment of pancreatic cancer. (1.4)

2 DOSAGE AND ADMINISTRATION

AVGEMSI is for intravenous use only.

- Ovarian Cancer: 1,000 mg/m^2 over 30 minutes on Days 1 and 8 of each 21-day cycle. (2.1)
- Breast Cancer: 1,250 mg/m^2 over 30 minutes on Days 1 and 8 of each 21-day cycle. (2.2)
- Non-Small Cell Lung Cancer: 1,000 mg/m^2 over 30 minutes on Days 1, 8, and 15 of each 28-day cycle or 1,250 mg/m^2 over 30 minutes on Days 1 and 8 of each 21-day cycle. (2.3)
- Pancreatic Cancer: 1,000 mg/m^2 over 30 minutes once weekly for the first 7 weeks, then one-week rest, then once weekly for 3 weeks of each 28-day cycle. (2.4)

3 DOSAGE FORMS AND STRENGTHS

Injection: 200 mg/5.26 mL,1 g/26.3 mL, and 2 g/52.6 mL(38 mg/mL) in a multiple-dose vial. (3)

4 CONTRAINDICATIONS

Patients with a known hypersensitivity to gemcitabine. (4)

5 WARNINGS AND PRECAUTIONS

- Schedule-Dependent Toxicity: Increased toxicity with infusion time greater than 60 minutes or dosing more frequently than once weekly. (5.1)
- Myelosuppression: Monitor for myelosuppression prior to each cycle and reduce or withhold dose for severe myelosuppression. (5.2)
- Severe Cutaneous Adverse Reactions (SCARs): Permanently discontinue AVGEMSI if SCARs occur. (5.3)
- Pulmonary Toxicity and Respiratory Failure: Discontinue AVGEMSI for unexplained dyspnea or other evidence of severe pulmonary toxicity. (5.4)
- Hemolytic Uremic Syndrome (HUS): Monitor renal function prior to initiation and during treatment. Discontinue AVGEMSI for HUS or severe renal impairment. (5.5)
- Hepatic Toxicity: Monitor hepatic function prior to initiation and during treatment. Discontinue AVGEMSI for severe hepatic toxicity. (5.6)
- Embryo-Fetal Toxicity: Can cause fetal harm. Advise females and males of reproductive potential to use effective contraception. (5.7, 8.1)
- Exacerbation of Radiation Therapy Toxicity: May cause severe and life-threatening toxicity when administered during or within 7 days of radiation therapy. (5.8)
- Capillary Leak Syndrome: Discontinue AVGEMSI. (5.9)
- Posterior Reversible Encephalopathy Syndrome (PRES): Discontinue AVGEMSI. (5.10)

6 ADVERSE REACTIONS

The most common adverse reactions for the single agent (≥20%) are nausea/vomiting, anemia, increased aspartate aminotransferase (AST), increased alanine aminotransferase (ALT), neutropenia, increased alkaline phosphatase, proteinuria, fever, hematuria, rash, thrombocytopenia, dyspnea, and edema. (6.1)

To report SUSPECTED ADVERSE REACTIONS, contact Avyxa Pharma, LLC at 1-888-520-0954 or FDA at 1-800-FDA-1088 or www.fda.gov/medwatch.

8 USE IN SPECIFIC POPULATIONS

Lactation: Advise not to breastfeed. (8.2)

FULL PRESCRIBING INFORMATION

1 INDICATIONS AND USAGE

1.1 Ovarian Cancer

AVGEMSI in combination with carboplatin is indicated for the treatment of patients with advanced ovarian cancer that has relapsed at least 6 months after completion of platinum-based therapy.

1.2 Breast Cancer

AVGEMSI in combination with paclitaxel is indicated for the first-line treatment of patients with metastatic breast cancer after failure of prior anthracycline-containing adjuvant chemotherapy, unless anthracyclines were clinically contraindicated.

1.3 Non-Small Cell Lung Cancer

AVGEMSI in combination with cisplatin is indicated for the first-line treatment of patients with inoperable, locally advanced (Stage IIIA or IIIB) or metastatic (Stage IV) non-small cell lung cancer (NSCLC).

1.4 Pancreatic Cancer

AVGEMSI is indicated as first-line treatment for patients with locally advanced (nonresectable Stage II or Stage III) or metastatic (Stage IV) adenocarcinoma of the pancreas. AVGEMSI is indicated for patients previously treated with fluorouracil.

2 DOSAGE AND ADMINISTRATION

2.1 Ovarian Cancer

Recommended Dose and Schedule

The recommended dosage of AVGEMSI is 1,000 mg/m^2 intravenously over 30 minutes on Days 1 and 8 of each 21-day cycle, in combination with carboplatin AUC 4 administered intravenously on Day 1 after AVGEMSI administration. Refer to carboplatin prescribing information for additional information.

Dosage Modifications

Recommended dosage modifications for AVGEMSI for myelosuppression are described in Tables 1 and 2 [see Warnings and Precautions (5.2)]. Refer to the recommended dosage modifications for non-hematologic adverse reactions [see Dosage and Administration (2.5)].

Table 1: Recommended Dosage Modifications for AVGEMSI for Myelosuppression on Day of Treatment in Ovarian Cancer
Treatment Day | Absolute Neutrophil Count; (x 10^6/L) |  | Platelet Count; (x 10^6/L) | Dosage Modification
Day 1 | Greater than or equal to 1,500 | And | Greater than or equal to 100,000 | None
Day 1 | Less than 1,500 | Or | Less than 100,000 | Delay Treatment Cycle
Day 8 | Greater than or equal to 1,500 | And | Greater than or equal to 100,000 | None
Day 8 | 1,000 to 1,499 | Or | 75,000 to 99,999 | 50% of full dose
 | Less than 1,000 | Or | Less than 75,000 | Hold

Table 2: Recommended Dosage Modifications for AVGEMSI for Myelosuppression in Previous Cycle in Ovarian Cancer
Occurrence | Myelosuppression During Treatment Cycle | Dosage Modification
Initial Occurrence | - Absolute neutrophil count less than 500 x 10^6/L for more than 5 days or - Absolute neutrophil count less than 100 x 10^6/L for more than 3 days or - Febrile neutropenia or - Platelets less than 25,000 x 10^6/L - Cycle delay for more than one week due to toxicity | Permanently reduce AVGEMSI to 800 mg/m^2 on Days 1 and 8
Subsequent Occurrence | If any of the above toxicities occur after the initial dose reduction | Permanently reduce AVGEMSI to 800 mg/m^2 on Days 1 only

2.2 Breast Cancer

Recommended Dose and Schedule

The recommended dosage of AVGEMSI is 1,250 mg/m^2 intravenously over 30 minutes on Days 1 and 8 of each 21-day cycle in combination with paclitaxel 175 mg/m^2 on Day 1 before AVGEMSI administration. Refer to paclitaxel prescribing information for additional information.

Dosage Modifications

Recommended dosage modifications for AVGEMSI for myelosuppression are described in Table 3 [see Warnings and Precautions (5.2)]. Refer to the recommended dosage modifications for non-hematologic adverse reactions [see Dosage and Administration (2.5)].

Table 3: Recommended Dosage Modifications for AVGEMSI for Myelosuppression on Day of Treatment in Breast Cancer
Treatment Day | Absolute Neutrophil Count; (x 10^6/L) |  | Platelet Count (x 10^6/L) | Dosage Modification
Day 1 | Greater than or equal to 1,500 | And | Greater than or equal to 100,000 | None
Day 1 | Less than 1,500 | Or | Less than 100,000 | Hold
Day 8 | Greater than or equal to 1,200 | And | Greater than 75,000 | None
Day 8 | 1,000 to 1,199 | Or | 50,000 to 75,000 | 75% of full dose
 | 700 to 999 | And | Greater than or equal to 50,000 | 50% of full dose
 | Less than 700 | Or | Less than 50,000 | Hold

2.3 Non-Small Cell Lung Cancer

Recommended Dose and Schedule

28-day schedule

The recommended dosage of AVGEMSI is 1,000 mg/m^2 intravenously over 30 minutes on Days 1, 8, and 15 of each 28-day cycle in combination with cisplatin 100 mg/m^2 administered intravenously on Day 1 after AVGEMSI administration.

21-day schedule

The recommended dosage of AVGEMSI is 1,250 mg/m^2 intravenously over 30 minutes on Days 1 and 8 of each 21-day cycle in combination with cisplatin 100 mg/m^2 administered intravenously on Day 1 after AVGEMSI administration.

Refer to cisplatin prescribing information for additional information.

Dosage Modifications

Recommended dosage modifications for AVGEMSI myelosuppression are described in Table 4 [see Warnings and Precautions (5.2)]. Refer to the recommended dosage modifications for non-hematologic adverse reactions [see Dosage and Administration (2.5)].

2.4 Pancreatic Cancer

Recommended Dose and Schedule

The recommended dosage of AVGEMSI is 1,000 mg/m^2 intravenously over 30 minutes. The recommended treatment schedule is as follows:

- Weeks 1 to 8: weekly dosing for the first 7 weeks followed by one-week rest.
- After week 8: weekly dosing on Days 1, 8, and 15 of each 28-day cycle.

Dosage Modifications

Recommended dosage modifications for AVGEMSI for myelosuppression are described in Table 4 [see Warnings and Precautions (5.2)]. Refer to the recommended dosage modifications for non-hematologic adverse reactions [see Dosage and Administration (2.5)].

Table 4: Recommended Dosage Modifications for AVGEMSI for Myelosuppression in Pancreatic Cancer and Non-Small Cell Lung Cancer
Absolute Neutrophil Count (x 10^6/L) |  | Platelet Count; (x 10^6/L) | Dosage Modification
Greater than or equal to 1,000 | And | Greater than or equal to 100,000 | None
500 to 999 | Or | 50,000 to 99,999 | 75% of full dose
Less than 500 | Or | Less than 50,000 | Hold

2.5 Dosage Modifications for Non-Hematologic Adverse Reactions

Permanently discontinue AVGEMSI for any of the following:

- Severe Cutaneous Adverse Reactions (SCARs) [see Warnings and Precautions (5.3)]
- Unexplained dyspnea or evidence of severe pulmonary toxicity [see Warnings and Precautions (5.4)]
- Hemolytic uremic syndrome (HUS) or severe renal impairment [see Warnings and Precautions (5.5)]
- Severe hepatic toxicity [see Warnings and Precautions (5.6)]
- Capillary leak syndrome (CLS) [see Warnings and Precautions (5.9)]
- Posterior reversible encephalopathy syndrome (PRES) [see Warnings and Precautions (5.10)]

Withhold AVGEMSI or reduce dose by 50% for other Grade 3 or 4 non-hematological adverse reactions until resolved. No dose modifications are recommended for alopecia, nausea, or vomiting.

2.6 Preparation

AVGEMSI is a hazardous drug. Follow applicable special handling and disposal procedures.^1 Exercise caution and wear gloves when preparing AVGEMSI solutions. Immediately wash the skin thoroughly or rinse the mucosa with copious amounts of water if AVGEMSI contacts the skin or mucus membranes. Death has occurred in animal studies due to dermal absorption.

After first use, store the partially used multiple-dose vial in the original carton, refrigerated at 2°C to 8°C (36ºF to 46°F) for up to 14 days. Discard unused portion of the multiple-dose vial after 14 days.

Preparation for Intravenous Infusion Administration

- Withdraw the calculated dose from the vial.
- Prior to administration, dilute the appropriate amount of drug with 0.9% Sodium Chloride Injection, USP to a minimum final concentration of at least 0.1 mg/mL.
- Store diluted AVGEMSI solution for no more than 24 hours at controlled room temperature of 20°C to 25°C (68°F to 77°F) [see USP Controlled Room Temperature]. Discard AVGEMSI solution if not used within 24 hours after dilution.
- Visually inspect for particulate matter or discoloration prior to administration and discard if particulate matter or discoloration is observed.
- No incompatibilities have been observed with infusion bottles or polyvinyl chloride bags and administration sets.

3 DOSAGE FORMS AND STRENGTHS

Injection: 200 mg/5.26 mL (38 mg/mL), 1 g/26.3 mL (38 mg/mL), and 2 g/52.6 mL (38 mg/mL) as a clear and colorless to light straw-colored solution in a multiple-dose vial.

4 CONTRAINDICATIONS

AVGEMSI is contraindicated in patients with a known hypersensitivity to gemcitabine. Reactions include anaphylaxis [see Adverse Reactions (6.1)].

5 WARNINGS AND PRECAUTIONS

5.1 Schedule-Dependent Toxicity

In clinical trials evaluating the maximum tolerated dose of gemcitabine, prolongation of the infusion time beyond 60 minutes or more frequent than weekly dosing resulted in an increased incidence of clinically significant hypotension, severe flu-like symptoms, myelosuppression, and asthenia. The half-life of gemcitabine is influenced by the length of the infusion [see Clinical Pharmacology (12.3)]. Refer to the recommended AVGEMSI dosage [see Dosage and Administration (2.1, 2.2, 2.3, 2.4)].

5.2 Myelosuppression

Myelosuppression manifested by neutropenia, thrombocytopenia, and anemia, occurs with gemcitabine as a single agent and the risks are increased when gemcitabine is combined with other cytotoxic drugs. In clinical trials, Grade 3-4 neutropenia, anemia, and thrombocytopenia occurred in 25%, 8%, and 5%, respectively of the 979 patients who received single agent gemcitabine. The frequencies of Grade 3-4 neutropenia, anemia, and thrombocytopenia varied from 48% to 71%, 8% to 28%, and 5% to 55%, respectively, in patients receiving gemcitabine in combination with another drug [see Adverse Reactions (6.1)].

Prior to each dose of AVGEMSI, obtain a complete blood count (CBC) with a differential and a platelet count. Modify the dosage as recommended [see Dosage and Administration (2.1, 2.2, 2.3, 2.4)].

5.3 Severe Cutaneous Adverse Reactions (SCARs)

SCARs, including Stevens-Johnson syndrome (SJS), toxic epidermal necrolysis (TEN), drug reaction with eosinophilia and systemic symptoms (DRESS), and acute generalized exanthematous pustulosis (AGEP), which can be life-threatening or fatal, have been reported in association with gemcitabine treatment [see Adverse Reactions (6.2)]. Monitor patients for signs and symptoms of severe cutaneous adverse reactions. Permanently discontinue gemcitabine in patients who develop SCARs.

5.4 Pulmonary Toxicity and Respiratory Failure

Pulmonary toxicity, including interstitial pneumonitis, pulmonary fibrosis, pulmonary edema, and adult respiratory distress syndrome (ARDS), has been reported. In some cases, these pulmonary events can lead to fatal respiratory failure despite the discontinuation of therapy. The onset of pulmonary symptoms may occur up to 2 weeks after the last dose of gemcitabine [see Adverse Reactions (6.1, 6.2)].

Permanently discontinue AVGEMSI in patients who develop unexplained dyspnea, with or without bronchospasm, or evidence of severe pulmonary toxicity.

5.5 Hemolytic Uremic Syndrome

Hemolytic uremic syndrome (HUS), including fatalities from renal failure or the requirement for dialysis, can occur with gemcitabine. In clinical trials, HUS occurred in 0.25% of 2429 patients. Most fatal cases of renal failure were due to HUS [see Adverse Reactions (6.1)]. Serious cases of thrombotic microangiopathy other than HUS have been reported with gemcitabine [see Adverse Reactions (6.2)].

Assess renal function prior to initiation of AVGEMSI and periodically during treatment. Consider the diagnosis of HUS in patients who develop anemia with evidence of microangiopathic hemolysis; increased bilirubin or LDH; reticulocytosis; severe thrombocytopenia; or evidence of renal failure (increased serum creatinine or BUN). Permanently discontinue AVGEMSI in patients with HUS or severe renal impairment. Renal failure may not be reversible even with the discontinuation of therapy.

5.6 Hepatic Toxicity

Drug-induced liver injury, including liver failure and death, has been reported in patients receiving gemcitabine alone or with other potentially hepatotoxic drugs [see Adverse Reactions (6.1, 6.2)]. Administration of gemcitabine in patients with concurrent liver metastases or a pre-existing medical history of hepatitis, alcoholism, or liver cirrhosis can lead to exacerbation of the underlying hepatic insufficiency. Assess hepatic function prior to initiation of AVGEMSI and periodically during treatment. Permanently discontinue AVGEMSI in patients who develop severe hepatic toxicity.

5.7 Embryo-Fetal Toxicity

Based on animal data and its mechanism of action, AVGEMSI can cause fetal harm when administered to a pregnant woman. Gemcitabine was teratogenic, embryotoxic, and fetotoxic in mice and rabbits.

Advise pregnant women of the potential risk to a fetus. Advise females of reproductive potential to use effective contraception during treatment with AVGEMSI and for 6 months after the final dose. Advise male patients with female partners of reproductive potential to use effective contraception during treatment with AVGEMSI and for 3 months following the final dose [see Use in Specific Populations (8.1, 8.3)].

5.8 Exacerbation of Radiation Therapy Toxicity

Gemcitabine is not recommended for use in combination with radiation therapy.

Concurrent (given together or ≤7 days apart)

Life-threatening mucositis, especially esophagitis and pneumonitis occurred in a trial in which gemcitabine was administered at a dose of 1000 mg/m^2 to patients with non-small cell lung cancer for up to 6 consecutive weeks concurrently with thoracic radiation.

Non-concurrent (given >7 days apart)

Excessive toxicity has not been observed when gemcitabine is administered more than 7 days before or after radiation. Radiation recall has been reported in patients who received gemcitabine after prior radiation.

5.9 Capillary Leak Syndrome

Capillary leak syndrome (CLS) with severe consequences has been reported in patients receiving gemcitabine as a single agent or in combination with other chemotherapeutic agents [see Adverse Reactions (6.2)]. Permanently discontinue AVGEMSI if CLS develops during therapy.

5.10 Posterior Reversible Encephalopathy Syndrome

Posterior reversible encephalopathy syndrome (PRES) has been reported in patients receiving gemcitabine as a single agent or in combination with other chemotherapeutic agents [see Adverse Reactions (6.2)]. PRES can present with headache, seizure, lethargy, hypertension, confusion, blindness, and other visual and neurologic disturbances. Confirm the diagnosis of PRES with magnetic resonance imaging (MRI). Permanently discontinue AVGEMSI if PRES develops during therapy.

6 ADVERSE REACTIONS

The following clinically significant adverse reactions are described elsewhere in the labeling:

- Hypersensitivity [see Contraindications (4)]
- Schedule-Dependent Toxicity [see Warnings and Precautions (5.1)]
- Myelosuppression [see Warnings and Precautions (5.2)]
- Severe Cutaneous Adverse Reactions [see Warnings and Precautions (5.3)]
- Pulmonary Toxicity and Respiratory Failure [see Warnings and Precautions (5.4)]
- Hemolytic Uremic Syndrome [see Warnings and Precautions (5.5)]
- Hepatic Toxicity [see Warnings and Precautions (5.6)]
- Exacerbation of Radiation Therapy Toxicity [see Warnings and Precautions (5.8)]
- Capillary Leak Syndrome [see Warnings and Precautions (5.9)]
- Posterior Reversible Encephalopathy Syndrome [see Warnings and Precautions (5.10)]

6.1 Clinical Trials Experience

Because clinical trials are conducted under widely varying conditions, adverse reaction rates observed in the clinical trials of a drug cannot be directly compared to rates in the clinical trials of another drug and may not reflect the rates observed in practice.

Single Agent

The data described below reflect exposure to gemcitabine as a single agent administered at doses between 800 mg/m^2 to 1250 mg/m^2 intravenously over 30 minutes once weekly in 979 patients with various malignancies. The most common (≥20%) adverse reactions of single agent gemcitabine are nausea/vomiting, anemia, increased alanine aminotransferase (ALT), increased aspartate aminotransferase (AST), neutropenia, increased alkaline phosphatase, proteinuria, fever, hematuria, rash, thrombocytopenia, dyspnea, and edema. The most common (≥5%) Grade 3 or 4 adverse reactions were neutropenia, nausea/vomiting, increased ALT, increased alkaline phosphatase, anemia, increased AST, and thrombocytopenia. Approximately 10% of the 979 patients discontinued gemcitabine due to adverse reactions. Adverse reactions resulting in discontinuation of gemcitabine in 2% of 979 patients were cardiovascular adverse reactions (myocardial infarction, cerebrovascular accident, arrhythmia, and hypertension) and adverse reactions resulting in discontinuation of gemcitabine in <1% of 979 patients were anemia, thrombocytopenia, hepatic dysfunction, renal dysfunction, nausea/vomiting, fever, rash, dyspnea, hemorrhage, infection, stomatitis, somnolence, flu-like syndrome, and edema.

Tables 5 and 6 present the incidence of selected adverse reactions and laboratory abnormalities reported in patients with various malignancies receiving single agent gemcitabine across 5 clinical trials. Additional clinically significant adverse reactions are provided following Table 6.

Table 5: Selected Adverse Reactions Occurring in ≥10% of Patients Receiving Single Agent Gemcitabinea
Adverse Reactionsb | Gemcitabinec
Adverse Reactionsb | All Grades; (%) | Grade 3; (%) | Grade 4; (%)
Nausea and Vomiting | 69 | 13 | 1
Fever | 41 | 2 | 0
Rash | 30 | <1 | 0
Dyspnea | 23 | 3 | <1
Diarrhea | 19 | 1 | 0
Hemorrhage | 17 | <1 | <1
Infection | 16 | 1 | <1
Alopecia | 15 | <1 | 0
Stomatitis | 11 | <1 | 0
Somnolence | 11 | <1 | <1
Paresthesias | 10 | <1 | 0
a Grade based on criteria from the World Health Organization (WHO).
b For approximately 60% of patients, non-laboratory adverse reactions were graded only if assessed to be possibly drug-related.
c N=699-974; all patients with laboratory or non-laboratory data.

Table 6: Selected Laboratory Abnormalities Occurring in Patients Receiving Single Agent Gemcitabinea
Laboratory Abnormalityb | Gemcitabinec
Laboratory Abnormalityb | All Grades; (%) | Grade 3; (%) | Grade 4; (%)
Hematologic
Anemia | 68 | 7 | 1
Neutropenia | 63 | 19 | 6
Thrombocytopenia | 24 | 4 | 1
Hepatic
Increased ALT | 68 | 8 | 2
Increased AST | 67 | 6 | 2
Increased Alkaline Phosphatase | 55 | 7 | 2
Hyperbilirubinemia | 13 | 2 | <1
Renal
Proteinuria | 45 | <1 | 0
Hematuria | 35 | <1 | 0
Increased BUN | 16 | 0 | 0
Increased Creatinine | 8 | <1 | 0
a Grade based on criteria from the WHO.
b Regardless of causality.
c N=699-974; all patients with laboratory or non-laboratory data.

Additional adverse reactions include the following:

- Transfusion requirements: Red blood cell transfusions (19%); platelet transfusions (<1%)
- Edema: Edema (13%), peripheral edema (20%), generalized edema (<1%)
- Flu-like symptoms: Fever, asthenia, anorexia, headache, cough, chills, myalgia, insomnia, rhinitis, sweating, and/or malaise (19%)
- Infection: Sepsis (<1%)
- Extravasation: Injection-site reactions (4%)
- Allergic: Bronchospasm (<2%); anaphylactoid reactions

Ovarian Cancer

Tables 7 and 8 present the incidence of selected adverse reactions and laboratory abnormalities, occurring in ≥10% of gemcitabine-treated patients and at a higher incidence in the gemcitabine with carboplatin arm, reported in a randomized trial (Study 1) of gemcitabine with carboplatin (n=175) compared to carboplatin alone (n=174) for the second-line treatment of ovarian cancer in women with disease that had relapsed more than 6 months following first-line platinum-based chemotherapy [see Clinical Studies (14.1)]. Additional clinically significant adverse reactions, occurring in <10% of patients, are provided following Table 8.

The proportion of patients with dose adjustments for carboplatin (1.8% versus 3.8%), doses of carboplatin omitted (0.2% versus 0) and discontinuing treatment for adverse reactions (11% versus 10%), were similar between arms. Dose adjustment for gemcitabine occurred in 10% of patients and gemcitabine dose was omitted in 14% of patients in the gemcitabine /carboplatin arm.

Table 7: Adverse Reactions Occurring in >10% of Patients Receiving Gemcitabine with Carboplatin and at Higher Incidence than in Patients Receiving Single Agent Carboplatin [Between Arm Difference of ≥5% (All Grades) or ≥2% (Grades 3-4)] in Study 1a
Adverse Reactionsb | Gemcitabine/Carboplatin (N = 175) |  |  | Carboplatin (N=174)
Adverse Reactionsb | All Grades (%) | Grade 3 (%) | Grade 4 (%) | All Grades (%) | Grade 3 (%) | Grade 4 (%)
Nausea | 69 | 6 | 0 | 61 | 3 | 0
Alopecia | 49 | 0 | 0 | 17 | 0 | 0
Vomiting | 46 | 6 | 0 | 36 | 2 | <1
Constipation | 42 | 6 | 1 | 37 | 3 | 0
Fatigue | 40 | 3 | <1 | 32 | 5 | 0
Diarrhea | 25 | 3 | 0 | 14 | <1 | 0
Stomatitis/Pharyngitis | 22 | <1 | 0 | 13 | 0 | 0
a Grade based on National Cancer Institute CTC Version 2.0.
b Regardless of causality.

Table 8: Laboratory Abnormalities Occurring in Patients Receiving Gemcitabine with Carboplatin and at Higher Incidence than in Patients Receiving Single Agent Carboplatin [Between Arm Difference of ≥5% (All Grades) or ≥2% (Grades 3-4)] in Study 1a
Laboratory Abnormalityb | Gemcitabine/Carboplatin (N = 175) |  |  | Carboplatin (N=174)
Laboratory Abnormalityb | All Grades (%) | Grade 3 (%) | Grade 4 (%) | All Grades (%) | Grade 3 (%) | Grade 4 (%)
Hematologic
Neutropenia | 90 | 42 | 29 | 58 | 11 | 1
Anemia | 86 | 22 | 6 | 75 | 9 | 2
Thrombocytopenia | 78 | 30 | 5 | 57 | 10 | 1
RBC Transfusionsc | 38 | - | - | 15 | - | -
Platelet Transfusionsc | 9 | - | - | 3 | - | -
a Grade based on National Cancer Institute CTC Version 2.0.
b Regardless of causality.
c Percent of patients receiving transfusions. Transfusions are not CTC-graded events. Blood transfusions included both packed red blood cells and whole blood.

Hematopoietic growth factors were administered more frequently in the gemcitabine-containing arm: leukocyte growth factor (24% and 10%) and erythropoiesis-stimulating agent (7% and 3.9%).

The following clinically relevant, Grade 3 and 4 adverse reactions occurred more frequently in the gemcitabine with carboplatin arm: dyspnea (3.4% versus 2.9%), febrile neutropenia (1.1% versus 0), hemorrhagic event (2.3% versus 1.1%), motor neuropathy (1.1% versus 0.6%), and rash/desquamation (0.6% versus 0).

Breast Cancer

Tables 9 and 10 present the incidence of selected adverse reactions and laboratory abnormalities, occurring in ≥10% of gemcitabine-treated patients and at a higher incidence in the gemcitabine with paclitaxel arm, reported in a randomized trial (Study 2) of gemcitabine with paclitaxel (n=262) compared to paclitaxel alone (n=259) for the first-line treatment of metastatic breast cancer (MBC) in women who received anthracycline-containing chemotherapy in the adjuvant/neo-adjuvant setting or for whom anthracyclines were contraindicated [see Clinical Studies (14.2)]. Additional clinically significant adverse reactions, occurring in <10% of patients, are provided following Table 10.

The requirement for dose reduction of paclitaxel were higher for patients in the gemcitabine /paclitaxel arm (5% versus 2%). The number of paclitaxel doses omitted (<1%), the proportion of patients discontinuing treatment for adverse reactions (7% versus 5%) and the number of treatment-related deaths (1 patient in each arm) were similar between the two arms.

Table 9: Selected Adverse Reactions Occurring in Patients Receiving Gemcitabine with Paclitaxel and at Higher Incidence than in Patients Receiving Single Agent Paclitaxel [Between Arm Difference of ≥5% (All Grades) or ≥2% (Grades 3-4)] in Study 2a
Adverse Reactionsb | Gemcitabine/Paclitaxel (N=262) |  |  | Paclitaxel (N=259)
Adverse Reactionsb | All Grades (%) | Grade 3 (%) | Grade 4 (%) | All Grades (%) | Grade 3 (%) | Grade 4 (%)
Alopecia | 90 | 14 | 4 | 92 | 19 | 3
Neuropathy-Sensory | 64 | 5 | <1 | 58 | 3 | 0
Nausea | 50 | 1 | 0 | 31 | 2 | 0
Fatigue | 40 | 6 | <1 | 28 | 1 | <1
Vomiting | 29 | 2 | 0 | 15 | 2 | 0
Diarrhea | 20 | 3 | 0 | 13 | 2 | 0
Anorexia | 17 | 0 | 0 | 12 | <1 | 0
Neuropathy-Motor | 15 | 2 | <1 | 10 | <1 | 0
Stomatitis/Pharyngitis | 13 | 1 | <1 | 8 | <1 | 0
Fever | 13 | <1 | 0 | 3 | 0 | 0
Rash/Desquamation | 11 | <1 | <1 | 5 | 0 | 0
Febrile Neutropenia | 6 | 5 | <1 | 2 | 1 | 0
a Grade based on National Cancer Institute CTC Version 2.0.
b Non-laboratory events were graded only if assessed to be possibly drug-related.

Table 10: Selected Laboratory Abnormalities Occurring in >10% of Patients Receiving Gemcitabine with Paclitaxel and at a Higher Incidence than Patients Receiving Single Agent Paclitaxel [Between Arm Difference of ≥5% (All Grades) or ≥2% (Grades 3-4)] in Study 2a
Laboratory Abnormalityb | Gemcitabine/Paclitaxel (N = 262) |  |  | Paclitaxel (N=259)
Laboratory Abnormalityb | All Grades (%) | Grade 3 (%) | Grade 4 (%) | All Grades (%) | Grade 3 (%) | Grade 4 (%)
Hematologic
Anemia | 69 | 6 | 1 | 51 | 3 | <1
Neutropenia | 69 | 31 | 17 | 31 | 4 | 7
Thrombocytopenia | 26 | 5 | <1 | 7 | <1 | <1
Hepatobiliary
Increased ALT | 18 | 5 | <1 | 6 | <1 | 0
Increased AST | 16 | 2 | 0 | 5 | <1 | 0
a Grade based on National Cancer Institute CTC Version 2.0.
b Regardless of causality.

Clinically relevant Grade 3 or 4 dyspnea occurred with a higher incidence in the gemcitabine with paclitaxel arm compared with the paclitaxel arm (1.9% versus 0).

Non-Small Cell Lung Cancer

Tables 11 and 12 present the incidence of selected adverse reactions and laboratory abnormalities, occurring in ≥10% of gemcitabine-treated patients and at a higher incidence in the gemcitabine with cisplatin arm, reported in a randomized trial (Study 3) of gemcitabine with cisplatin (n=260) administered in 28-day cycles as compared to cisplatin alone (n=262) in patients receiving first-line treatment for locally advanced or metastatic NSCLC [see Clinical Studies (14.3)].

Patients randomized to gemcitabine with cisplatin received a median of 4 cycles of treatment and those randomized to cisplatin alone received a median of 2 cycles of treatment. In this trial, the requirement for dose adjustments (>90% versus 16%), discontinuation of treatment for adverse reactions (15% versus 8%), and the proportion of patients hospitalized (36% versus 23%) were all higher for patients receiving gemcitabine with cisplatin compared to those receiving cisplatin alone. The incidence of febrile neutropenia (3% versus <1%), sepsis (4% versus 1%), Grade 3 cardiac dysrhythmias (3% versus <1%) were all higher in the gemcitabine with cisplatin arm compared to the cisplatin alone arm. The two-drug combination was more myelosuppressive with 4 (1.5%) possibly treatment-related deaths, including 3 resulting from myelosuppression with infection and one case of renal failure associated with pancytopenia and infection. No deaths due to treatment were reported on the cisplatin arm.

Table 11: Selected Adverse Reactions Occurring in ≥10% of Patients Receiving Gemcitabine with Cisplatin and at Higher Incidence than in Patients Receiving Single Agent Cisplatin [Between Arm Difference of ≥5% (All Grades) or ≥2% (Grades 3-4)] in Study 3a
Adverse Reactionsb | Gemcitabine/Cisplatinc |  |  | Cisplatind
Adverse Reactionsb | All Grades; (%) | Grade 3; (%) | Grade 4 (%) | All Grades (%) | Grade 3; (%) | Grade 4; (%)
Nausea | 93 | 25 | 2 | 87 | 20 | <1
Vomiting | 78 | 11 | 12 | 71 | 10 | 9
Alopecia | 53 | 1 | 0 | 33 | 0 | 0
Neuro Motor | 35 | 12 | 0 | 15 | 3 | 0
Diarrhea | 24 | 2 | 2 | 13 | 0 | 0
Neuro Sensory | 23 | 1 | 0 | 18 | 1 | 0
Infection | 18 | 3 | 2 | 12 | 1 | 0
Fever | 16 | 0 | 0 | 5 | 0 | 0
Neuro Cortical | 16 | 3 | 1 | 9 | 1 | 0
Neuro Mood | 16 | 1 | 0 | 10 | 1 | 0
Local | 15 | 0 | 0 | 6 | 0 | 0
Neuro Headache | 14 | 0 | 0 | 7 | 0 | 0
Stomatitis | 14 | 1 | 0 | 5 | 0 | 0
Hemorrhage | 14 | 1 | 0 | 4 | 0 | 0
Hypotension | 12 | 1 | 0 | 7 | 1 | 0
Rash | 11 | 0 | 0 | 3 | 0 | 0
a Grade based on National Cancer Institute Common Toxicity Criteria (CTC).
b Non-laboratory events were graded only if assessed to be possibly drug-related.
c N=217-253; all gemcitabine/cisplatin patients with laboratory or non-laboratory data.
d N=213-248; all cisplatin patients with laboratory or non-laboratory data.

Table 12: Selected Laboratory Abnormalities Occurring in >10% of Patients Receiving Gemcitabine with Cisplatin and at Higher Incidence than in Patients Receiving Single Agent Cisplatin [Between Arm Difference of ≥5% (All Grades) or ≥2% (Grades 3-4)] in Study 3a
Laboratory Abnormalityb | Gemcitabine/Cisplatinc |  |  | Cisplatind
Laboratory Abnormalityb | All Grades (%) | Grade 3 (%) | Grade 4 (%) | All Grades (%) | Grade 3 (%) | Grade 4 (%)
Hematologic
Anemia | 89 | 22 | 3 | 67 | 6 | 1
Thrombocytopenia | 85 | 25 | 25 | 13 | 3 | 1
Neutropenia | 79 | 22 | 35 | 20 | 3 | 1
Lymphopenia | 75 | 25 | 18 | 51 | 12 | 5
RBC Transfusionse | 39 | - | - | 13 | - | -
Platelet Transfusionse | 21 | - | - | <1 | - | -
Hepatic
Increased Transaminases | 22 | 2 | 1 | 10 | 1 | 0
Increased Alkaline Phosphatase | 19 | 1 | 0 | 13 | 0 | 0
Renal
Increased Creatinine | 38 | 4 | <1 | 31 | 2 | <1
Proteinuria | 23 | 0 | 0 | 18 | 0 | 0
Hematuria | 15 | 0 | 0 | 13 | 0 | 0
Other Laboratory
Hyperglycemia | 30 | 4 | 0 | 23 | 3 | 0
Hypomagnesemia | 30 | 4 | 3 | 17 | 2 | 0
Hypocalcemia | 18 | 2 | 0 | 7 | 0 | <1
a Grade based on National Cancer Institute CTC Version 2.0.
b Regardless of causality.
c N=217-253; all gemcitabine /cisplatin patients with laboratory or non-laboratory data.
d N=213-248; all cisplatin patients with laboratory or non-laboratory data.
e N=213-248; Percent of patients receiving transfusions. Percent transfusions are not CTC-graded events.

Tables 13 and 14 present the incidence of selected adverse reactions and laboratory abnormalities occurring in ≥10% of gemcitabine-treated patients and at a higher incidence in the gemcitabine with cisplatin arm, reported in a randomized trial (Study 4) of gemcitabine with cisplatin (n=69) administered in 21-day cycles as compared to etoposide with cisplatin (n=66) in patients receiving first-line treatment for locally advanced or metastatic NSCLC [see Clinical Studies (14.3)]. Additional clinically significant adverse reactions are provided following Table 14.

Patients in the gemcitabine/cisplatin (GC) arm received a median of 5 cycles and those in the etoposide/cisplatin (EC) arm received a median of 4 cycles. The majority of patients receiving more than one cycle of treatment required dose adjustments; 81% in the GC arm and 68% in the EC arm. The incidence of hospitalizations for adverse reactions was 22% in the GC arm and 27% in the EC arm. The proportion of patients who discontinued treatment for adverse reactions was higher in the GC arm (14% versus 8%). The proportion of patients who were hospitalized for febrile neutropenia was lower in the GC arm (7% versus 12%). There was one death attributed to treatment, a patient with febrile neutropenia and renal failure, which occurred in the GC arm.

Table 13: Selected Adverse Reactions in Patients Receiving Gemcitabine with Cisplatin in Study 4a
Adverse Reactionsb | Gemcitabine/Cisplatinc |  |  | Etoposide/Cisplatind
Adverse Reactionsb | All Grades (%) | Grade 3 (%) | Grade 4 (%) | All Grades (%) | Grade 3 (%) | Grade 4; (%)
Nausea and Vomiting | 96 | 35 | 4 | 86 | 19 | 7
Alopecia | 77 | 13 | 0 | 92 | 51 | 0
Paresthesias | 38 | 0 | 0 | 16 | 2 | 0
Infection | 28 | 3 | 1 | 21 | 8 | 0
Stomatitis | 20 | 4 | 0 | 18 | 2 | 0
Diarrhea | 14 | 1 | 1 | 13 | 0 | 2
Edemae | 12 | - | - | 2 | - | -
Rash | 10 | 0 | 0 | 3 | 0 | 0
Hemorrhage | 9 | 0 | 3 | 3 | 0 | 3
Fever | 6 | 0 | 0 | 3 | 0 | 0
Somnolence | 3 | 0 | 0 | 3 | 2 | 0
Flu-like Syndromee | 3 | - | - | 0 | - | -
Dyspnea | 1 | 0 | 1 | 3 | 0 | 0
a Grade based on criteria from the WHO.
b Non-laboratory events were graded only if assessed to be possibly drug-related. Pain data were not collected.
c N=67-69; all gemcitabine/cisplatin patients with laboratory or non-laboratory data.
d N=57-63; all Etoposide/cisplatin patients with laboratory or non-laboratory data.
e Flu-like syndrome and edema were not graded.

Table 14: Selected Laboratory Abnormalities Occurring in Patients Receiving Gemcitabine with Cisplatin in Study 4a
Laboratory Abnormalityb | Gemcitabine/Cisplatinc |  |  | Etoposide/Cisplatind
Laboratory Abnormalityb | All Grades (%) | Grade 3 (%) | Grade 4 (%) | All Grades (%) | Grade 3 (%) | Grade 4; (%)
Hematologic
Anemia | 88 | 22 | 0 | 77 | 13 | 2
Neutropenia | 88 | 36 | 28 | 87 | 20 | 56
Thrombocytopenia | 81 | 39 | 16 | 45 | 8 | 5
RBC Transfusionse | 29 | - | - | 21 | - | -
Platelet Transfusionse | 3 | - | - | 8 | - | -
Hepatic
Increased Alkaline Phosphatase | 16 | 0 | 0 | 11 | 0 | 0
Increased ALT | 6 | 0 | 0 | 12 | 0 | 0
Increased AST | 3 | 0 | 0 | 11 | 0 | 0
Renal
Hematuria | 22 | 0 | 0 | 10 | 0 | 0
Proteinuria | 12 | 0 | 0 | 5 | 0 | 0
Increased BUN | 6 | 0 | 0 | 4 | 0 | 0
Increased Creatinine | 2 | 0 | 0 | 2 | 0 | 0
a Grade based on criteria from the WHO.
b Regardless of causality.
c N=67-69; all gemcitabine /cisplatin patients with laboratory or non-laboratory data.
d N=57-63; all Etoposide/cisplatin patients with laboratory or non-laboratory data.
e WHO grading scale not applicable to proportion of patients with transfusions.

6.2 Postmarketing Experience

The following adverse reactions have been identified during postapproval use of gemcitabine. Because these reactions are reported voluntarily from a population of uncertain size, it is not always possible to reliably estimate their frequency or establish a causal relationship to drug exposure.

- Blood and Lymphatic System: Thrombotic microangiopathy (TMA)
- Cardiovascular: Congestive heart failure, myocardial infarction, arrhythmias, supraventricular arrhythmias
- Vascular: Peripheral vasculitis, gangrene, capillary leak syndrome
- Skin: Cellulitis; pseudocellulitis; severe cutaneous adverse reactions (SCARs), including Stevens-Johnson syndrome (SJS), toxic epidermal necrolysis (TEN), drug reaction with eosinophilia and systemic symptoms (DRESS), and acute generalized exanthematous pustulosis (AGEP); desquamation and bullous skin eruptions
- Hepatic: Hepatic failure, hepatic veno-occlusive disease
- Pulmonary: Interstitial pneumonitis, pulmonary fibrosis, pulmonary edema, adult respiratory distress syndrome (ARDS), pulmonary eosinophilia
- Nervous System: Posterior reversible encephalopathy syndrome (PRES)

8 USE IN SPECIFIC POPULATIONS

8.1 Pregnancy

Risk Summary

Based on animal data and its mechanism of action, AVGEMSI can cause fetal harm when administered to a pregnant woman [see Clinical Pharmacology (12.1)]. There are no available data on the use of gemcitabine in pregnant women. In animal reproduction studies, gemcitabine was teratogenic, embryotoxic, and fetotoxic in mice and rabbits (see Data). Advise pregnant women of the potential risk to a fetus [see Use in Specific Populations (8.3)].

In the U.S. general population, the estimated background risk of major birth defects and miscarriages in clinically recognized pregnancies is 2-4% and 15-20% respectively.

Data

Animal Data

Gemcitabine is embryotoxic in mice. Daily dosing of gemcitabine to pregnant mice increased the incidence of fetal malformations (cleft palate, incomplete ossification) at doses of 1.5 mg/kg/day [about 0.005 times the 1,000 mg/m^2 clinical dose based on body surface area (BSA)]. Gemcitabine is embryotoxic and fetotoxic in rabbits. Daily dosing of gemcitabine to pregnant rabbits resulted in fetotoxicity (decreased fetal viability, reduced litter sizes and developmental delays) and increased the incidence of fetal malformations (fused pulmonary artery, absence of gall bladder) at doses of 0.1 mg/kg/day (about 0.002 times the 1000 mg/m^2 clinical dose based on BSA).

8.2 Lactation

Risk Summary

There is no information regarding the presence of gemcitabine or its metabolites in human milk, or their effects on the breastfed infant or on milk production. Due to the potential for serious adverse reactions in breastfed infants from gemcitabine, advise women not to breastfeed during treatment with AVGEMSI and for at least one week following the last dose.

8.3 Females and Males of Reproductive Potential

AVGEMSI can cause fetal harm when administered to a pregnant woman [see Use in Specific Populations (8.1)].

Pregnancy Testing

Verify pregnancy status in females of reproductive potential prior to initiating AVGEMSI [see Use in Specific Populations (8.1)].

Contraception

Females

Because of the potential for genotoxicity and embryo-fetal toxicity, advise females of reproductive potential to use effective contraception during treatment with AVGEMSI and for 6 months after the final dose of AVGEMSI.

Males

Because of the potential for genotoxicity, advise males with female partners of reproductive potential to use effective contraception during treatment with AVGEMSI and for 3 months after the final dose [see Nonclinical Toxicology (13.1)].

Infertility

Males

Based on animal studies, AVGEMSI may impair fertility in males of reproductive potential [see Nonclinical Toxicology (13.1)]. It is not known whether these effects on fertility are reversible.

8.4 Pediatric Use

The safety and effectiveness of gemcitabine have not been established in pediatric patients.

The safety and pharmacokinetics of gemcitabine were evaluated in a trial in pediatric patients with refractory leukemia. The maximum tolerated dose was 10 mg/m^2/min for 360 minutes weekly for three weeks followed by a one-week rest period.

The safety and activity of gemcitabine were evaluated in a trial of pediatric patients with relapsed acute lymphoblastic leukemia (22 patients) and acute myelogenous leukemia (10 patients) at a dose of 10 mg/m^2/min administered over 360 minutes weekly for three weeks followed by a one-week rest period. Patients with M1 or M2 bone marrow on Day 28 who did not experience unacceptable toxicity were eligible to receive a maximum of one additional four-week course. Toxicities observed included myelosuppression, febrile neutropenia, increased serum transaminases, nausea, and rash/desquamation. No meaningful clinical activity was observed in this trial.

8.5 Geriatric Use

In clinical studies which enrolled 979 patients with various malignancies who received single agent gemcitabine, no overall differences in safety were observed between patients aged 65 and older and younger patients, with the exception of a higher rate of Grade 3-4 thrombocytopenia in older patients as compared to younger patients.

In a randomized trial in women with ovarian cancer (Study 1), 175 women received gemcitabine with carboplatin, of which 29% were age 65 years or older. Similar effectiveness was observed between older and younger women. There was significantly higher Grade 3-4 neutropenia in women 65 years of age or older [see Dosage and Administration (2.1)].

Gemcitabine clearance is affected by age; however, there are no recommended dose adjustments based on patients' age [see Clinical Pharmacology (12.3)].

8.6 Gender

Gemcitabine clearance is decreased in females [see Clinical Pharmacology (12.3)]. In single agent studies of gemcitabine, women, especially older women, were more likely not to proceed to a subsequent cycle and to experience Grade 3-4 neutropenia and thrombocytopenia [see Dosage and Administration (2.1, 2.2, 2.3, 2.4)].

10 OVERDOSAGE

There is no known antidote for overdoses of gemcitabine. Myelosuppression, paresthesias, and severe rash were the principal toxicities seen when a single dose as high as 5700 mg/m^2 was administered by intravenous infusion over 30 minutes every 2 weeks to several patients in a dose-escalation study. In the event of suspected overdose, monitor with appropriate blood counts and provide supportive therapy, as necessary.

11 DESCRIPTION

Gemcitabine is a nucleoside metabolic inhibitor. The chemical name of gemcitabine hydrochloride, is 2'-deoxy-2',2´-difluorocytidine monohydrochloride (β-isomer). The structural formula is as follows:

Gemcitabine hydrochloride, USP is a white to off-white solid with a molecular formula of C9H11F2N3O4 • HCl and a molecular weight of 299.66 g/mol. It is soluble in water, slightly soluble in methanol, and practically insoluble in ethanol and polar organic solvents.

AVGEMSI is a sterile solution in multiple-dose vials for intravenous use. Each vial contains 200 mg, 1 g, or 2 g of gemcitabine equivalent to 227.57 mg, 1.137 g, or 2.275 g of gemcitabine hydrochloride, USP. Each mL contains 38 mg of gemcitabine-free base in water for injection equivalent to 43.26 mg of gemcitabine hydrochloride, USP. Sodium hydroxide is used for pH adjustment.

12 CLINICAL PHARMACOLOGY

12.1 Mechanism of Action

Gemcitabine kills cells undergoing DNA synthesis and blocks the progression of cells through the G1/S-phase boundary. Gemcitabine is metabolized by nucleoside kinases to diphosphate (dFdCDP) and triphosphate (dFdCTP) nucleosides. Gemcitabine diphosphate inhibits ribonucleotide reductase, an enzyme responsible for catalyzing the reactions that generate deoxynucleoside triphosphates for DNA synthesis, resulting in reductions in deoxynucleotide concentrations, including dCTP. Gemcitabine triphosphate competes with dCTP for incorporation into DNA. The reduction in the intracellular concentration of dCTP by the action of the diphosphate enhances the incorporation of gemcitabine triphosphate into DNA (selfpotentiation). After the gemcitabine nucleotide is incorporated into DNA, only one additional nucleotide is added to the growing DNA strands which eventually results in the initiation of apoptotic cell death.

12.3 Pharmacokinetics

The pharmacokinetics of gemcitabine were examined in 353 patients, with various solid tumors. Pharmacokinetic parameters were derived using data from patients treated for varying durations of therapy given weekly with periodic rest weeks and using both short infusions (<70 minutes) and long infusions (70 to 285 minutes). The total gemcitabine dose varied from 500 mg/m^2 to 3600 mg/m^2.

Distribution

The volume of distribution was increased with infusion length. Volume of distribution of gemcitabine was 50 L/m^2 following infusions lasting <70 minutes. For long infusions, the volume of distribution rose to 370 L/m^2.

Gemcitabine pharmacokinetics are linear and are described by a 2-compartment model. Population pharmacokinetic analyses of combined single and multiple dose studies showed that the volume of distribution of gemcitabine was significantly influenced by duration of infusion and sex. Gemcitabine plasma protein binding is negligible.

Elimination

Metabolism

The active metabolite, gemcitabine triphosphate, can be extracted from peripheral blood mononuclear cells. The half-life of the terminal phase for gemcitabine triphosphate from mononuclear cells ranges from 1.7 to 19.4 hours.

Excretion

Gemcitabine disposition was studied in 5 patients who received a single 1000 mg/m^2 of radiolabeled drug as a 30-minute infusion. Within one (1) week, 92% to 98% of the dose was recovered, almost entirely in the urine. Gemcitabine (<10%) and the inactive uracil metabolite, 2´-deoxy-2´,2´-difluorouridine (dFdU), accounted for 99% of the excreted dose. The metabolite dFdU is also found in plasma.

Specific Populations

Geriatric Patients

Clearance of gemcitabine was affected by age. The lower clearance in geriatric patients results in higher concentrations of gemcitabine for any given dose. Differences in either clearance or volume of distribution based on patient characteristics or the duration of infusion result in changes in half-life and plasma concentrations. Table 15 shows plasma clearance and half-life of gemcitabine following short infusions for typical patients by age and sex.

Gemcitabine half-life for short infusions ranged from 42 to 94 minutes, and for long infusions varied from 245 to 638 minutes, depending on age and sex, reflecting a greatly increased volume of distribution with longer infusions.

Male and Female Patients

Females have lower clearance and longer half-lives than male patients as described in Table 15.

Table 15: Gemcitabine Clearance and Half-Life for the "Typical" Patient
Age | Clearance Men (L/hr/m^2) | Clearance Women (L/hr/m^2) | Half-Lifea Men (min) | Half-Lifea Women (min)
29 | 92.2 | 69.4 | 42 | 49
45 | 75.7 | 57.0 | 48 | 57
65 | 55.1 | 41.5 | 61 | 73
79 | 40.7 | 30.7 | 79 | 94
a Half-life for patients receiving a <70 minute infusion.

Patients with Renal Impairment

No clinical studies have been conducted with gemcitabine in patients with decreased renal function.

Patients with Hepatic Impairment

No clinical studies have been conducted with gemcitabine in patients with decreased hepatic function.

Drug Interaction Studies

When gemcitabine (1250 mg/m^2 on Days 1 and 8) and cisplatin (75 mg/m^2 on Day 1) were administered in patients with NSCLC, the clearance of gemcitabine on Day 1 was 128 L/hr/m^2 and on Day 8 was 107 L/hr/m^2. Data from patients with NSCLC demonstrate that gemcitabine and carboplatin given in combination does not alter the pharmacokinetics of gemcitabine or carboplatin compared to administration of either single agent; however, due to wide confidence intervals and small sample size, interpatient variability may be observed.

Data from patients with metastatic breast cancer shows that gemcitabine has little or no effect on the pharmacokinetics (clearance and half-life) of paclitaxel and paclitaxel has little or no effect on the pharmacokinetics of gemcitabine.

13 NONCLINICAL TOXICOLOGY

13.1 Carcinogenesis, Mutagenesis, Impairment of Fertility

Long-term animal studies to evaluate the carcinogenic potential of gemcitabine have not been conducted. Gemcitabine was mutagenic in an in vitro mouse lymphoma (L5178Y) assay and was clastogenic in an in vivo mouse micronucleus assay. Gemcitabine intraperitoneal doses of 0.5 mg/kg/day [about 1/700 the 1000 mg/m^2 clinical dose based on body surface area (BSA)] in male mice resulted in moderate to severe hypospermatogenesis, decreased fertility, and decreased implantations. In female mice, fertility was not affected but maternal toxicities were observed at 1.5 mg/kg/day administered intravenously (about 1/200 the 1000 mg/m^2 clinical dose based on BSA) and fetotoxicity or embryolethality was observed at 0.25 mg/kg/day administered intravenously (about 1/1300 the 1000 mg/m^2 clinical dose based on BSA).

14 CLINICAL STUDIES

14.1 Ovarian Cancer

The efficacy of gemcitabine was evaluated in a randomized trial (Study 1) conducted in women with advanced ovarian cancer that had relapsed at least 6 months after first-line platinum-based therapy. Patients were randomized to receive either gemcitabine 1000 mg/m^2on Days 1 and 8 of each 21-day cycle with carboplatin AUC 4 on Day 1 after gemcitabine administration (n=178) or carboplatin AUC 5 on Day 1 of each 21-day cycle (n=178). The major efficacy outcome measure was progression-free survival (PFS).

A total of 356 patients were enrolled. Demographics and baseline characteristics are shown in Table 16. Efficacy results are presented in Table 17 and Figure 1. The addition of gemcitabine to carboplatin resulted in statistically significant improvements in PFS and overall response rate. Approximately 75% of patients in each arm received additional chemotherapy for disease progression; 13 of 120 patients in the carboplatin alone arm received gemcitabine for treatment of disease progression. There was no significant difference in overall survival between the treatment arms.

Table 16: Baseline Demographics and Clinical Characteristics for Study 1
 | Gemcitabine/Carboplatin (N=178) | Carboplatin (N=178)
Median age, years | 59 | 58
Range | 36 to 78 | 21 to 81
Baseline ECOG performance status 0-1a | 94% | 95%
Disease Status
Evaluable | 8% | 3%
Bidimensionally measurable | 92% | 96%
Platinum-free intervalb
6-12 months | 40% | 40%
>12 months | 59% | 60%
First-line therapy
Platinum-taxane combination | 70% | 71%
Platinum-non-taxane combination | 29% | 28%
Platinum monotherapy | 1% | 1%
a 5 patients on AVGEMSI with carboplatin arm and 4 patients on carboplatin arm had no baseline Eastern Cooperative Oncology Group (ECOG) performance status.
b 2 patients on AVGEMSI with carboplatin arm and 1 patient on carboplatin arm had a platinum-free interval <6 months.

Table 17: Efficacy Results in Study 1
Efficacy Parameter | Gemcitabine/Carboplatin (N=178) | Carboplatin (N=178)
Progression-Free Survival
Median (95% CIa) in months | 8.6 (8.0, 9.7) | 5.8 (5.2, 7.1)
Hazard Ratio (95% CI) | 0.72 (0.57, 0.90)
p-valueb | p=0.0038
Overall Survival
Median (95% CI) in months | 18.0 (16.2, 20.3) | 17.3 (15.2, 19.3)
Hazard Ratio (95% CI) | 0.98 (0.78, 1.24)
p-valueb | p=0.8977
Overall Response Rate by Investigator Review | 47.2% | 30.9%
p-valuec | p=0.0016
CRd | 14.6% | 6.2%
PR with PRNMe | 32.6% | 24.7%
Overall Response Ratef by Independent Review | 46.3% | 35.6%
p-valuec | p=0.11
CRd | 9.1% | 4.0%
PR with PRNMe | 37.2% | 31.7%
a CI=confidence interval.
b Log rank, unadjusted.
c Chi square.
d CR = Complete Response.
e PR with PRNM = Partial response with partial response, non-measurable disease.
f Independently reviewed cohort - gemcitabine/carboplatin (n=121), carboplatin (n=101); independent reviewers unable to measure disease detected by sonography or physical exam.

Figure 1: Kaplan-Meier Curves for Progression-Free Survival in Study 1

14.2 Breast Cancer

The efficacy of gemcitabine was evaluated in a multinational, randomized, open-label trial (Study 2) conducted in women receiving initial treatment for metastatic breast cancer and who have received prior adjuvant/neoadjuvant anthracycline chemotherapy unless clinically contraindicated. Patients were randomized to receive gemcitabine 1250 mg/m^2 on Days 1 and 8 of each 21-day cycle with paclitaxel 175 mg/m^2 administered on Day 1 before gemcitabine administration (n=267) or paclitaxel 175 mg/m^2 on Day 1 of each 21-day cycle (n=262). The major efficacy outcome measure was time to documented disease progression.

A total of 529 patients were enrolled. Demographic and baseline characteristics were similar between treatment arms (Table 18).

Efficacy results are presented in Table 19 and Figure 2. The addition of gemcitabine to paclitaxel resulted in statistically significant improvement in time to documented disease progression and overall response rate compared to paclitaxel alone. There was no significant difference in overall survival.

Table 18: Baseline Demographics and Clinical Characteristics for Study 2
 | Gemcitabine/Paclitaxel (N=267) | Paclitaxel (N=262)
Median age (years) | 53 | 52
Range | 26 to 83 | 26 to 75
Metastatic disease | 97% | 97%
Baseline KPSa ≥90 | 70% | 74%
Number of tumor sites
1-2 | 57% | 59%
≥3 | 43% | 41%
Visceral disease | 73% | 73%
Prior anthracycline | 97% | 96%
a Karnofsky Performance Status.

Table 19: Efficacy Results in Study 2
Efficacy Parameter | Gemcitabine/Paclitaxel (N=267) | Paclitaxel (N=262)
Time to Documented Disease Progressiona
Median (95% CIa) in months | 5.2 (4.2, 5.6) | 2.9 (2.6, 3.7)
Hazard Ratio (95% CI) | 0.650 (0.524, 0.805)
p-value | P<0.0001
Overall Survivalb
Median (95% CI) in months | 18.6 (16.5, 20.7) | 15.8 (14.1, 17.3)
Hazard Ratio (95% CI) | 0.86 (0.71, 1.04)
p-value | Not Significant
Overall Response Rate | 40.8% | 22.1%
(95% CI) | (34.9, 46.7) | (17.1, 27.2)
p-value | P<0.0001
a These represent reconciliation of investigator and Independent Review Committee assessments according to a predefined algorithm.
b Based on the ITT population.

Figure 2: Kaplan-Meier Curves for Time to Documented Disease Progression in Study 2

14.3 Non-Small Cell Lung Cancer

The efficacy of gemcitabine was evaluated in two randomized, multicenter trials.

Study 3: 28-Day Schedule

A multinational, randomized trial (Study 3) compared gemcitabine with cisplatin to cisplatin alone in the treatment of patients with inoperable Stage IIIA, IIIB, or IV NSCLC who had not received prior chemotherapy. Patients were randomized to receive either gemcitabine 1000 mg/m^2 on Days 1, 8, and 15 of each 28-day cycle with cisplatin 100 mg/m^2 on Day 1 after gemcitabine administration (N=260) or cisplatin 100 mg/m^2 on Day 1 of each 28-day cycle (N=262). The major efficacy outcome measure was overall survival.

A total of 522 patients were enrolled. Demographics and baseline characteristics (Table 20) were similar between arms with the exception of histologic subtype of NSCLC, with 48% of patients on the cisplatin arm and 37% of patients on the gemcitabine with cisplatin arm having adenocarcinoma.

Efficacy results are presented in Table 21 and Figure 3.

Study 4: 21-Day Schedule

A randomized (1:1), multicenter trial (Study 4) was conducted in patients with Stage IIIB or IV NSCLC. Patients were randomized to receive gemcitabine 1250 mg/m^2 on Days 1 and 8 of each 21-day cycle with cisplatin 100 mg/m^2 on Day 1 after gemcitabine administration or etoposide 100 mg/m^2 intravenously on Days 1, 2, and 3 with cisplatin 100 mg/m^2 on Day 1 of each 21-day cycle. The major efficacy outcome measure was response rate.

A total of 135 patients were enrolled. Demographics and baseline characteristics are summarized in Table 20.

Efficacy results are presented in Table 21. There was no significant difference in survival between the two treatment arms. The median survival was 8.7 months for the gemcitabine with cisplatin arm versus 7 months for the etoposide with cisplatin arm. Median time to disease progression for the gemcitabine with cisplatin arm was 5 months compared to 4.1 months on the etoposide with cisplatin arm (Log rank p=0.015, two-sided). The objective response rate for the gemcitabine with cisplatin arm was 33% compared to 14% on the etoposide with cisplatin arm (Fisher's Exact p=0.01, two-sided).

Table 20: Baseline Demographics and Clinical Characteristics for Studies 3 and 4
Trial | 28-day Schedule (Study 3) |  | 21-day Schedule (Study 4)
 | Gemcitabine/ Cisplatin (N=260) | Cisplatin (N=262) | Gemcitabine/ Cisplatin (N=69) | Etoposide/ Cisplatin (N=66)
Male | 70% | 71% | 93% | 92%
Median age, years | 62 | 63 | 58 | 60
Range | 36 to 88 | 35 to 79 | 33 to 76 | 35 to 75
Stage IIIA | 7% | 7% | N/Aa | N/Aa
Stage IIIB | 26% | 23% | 48% | 52%
Stage IV | 67% | 70% | 52% | 49%
Baseline KPSb 70 to 80 | 41% | 44% | 45% | 52%
Baseline KPSb | 57% | 55% | 55% | 49%
a N/A Not applicable.
b Karnofsky Performance Status.

Table 21: Efficacy Results for Studies 3 and 4
Trial | 28-day Schedule (Study 3) |  | 21-day Schedule (Study 4)
Efficacy Parameter | Gemcitabine/Cisplatin (N=260) | Cisplatin (N=262) | Gemcitabine/ Cisplatin (N=69) | Etoposide/ Cisplatin (N=66)
Survival
Median (95% CIa) in months | 9.0 (8.2, 11.0) | 7.6 (6.6, 8.8) | 8.7 (7.8, 10.1) | 7.0 (6.0, 9.7)
p-valueb | p=0.008 |  | p=0.18
Time to Disease Progression
Median (95% CIa) in months | 5.2 (4.2, 5.7) | 3.7 (3.0, 4.3) | 5.0 (4.2, 6.4) | 4.1 (2.4, 4.5)
p-valueb | p=0.009 |  | p=0.015
Tumor Response | 26% | 10% | 33% | 14%
p-valueb | P<0.0001 |  | p=0.01
a CI=confidence intervals.
b p-value two-sided Fisher's Exact test for difference in binomial proportions; log rank test for time-to-event analyses.

Figure 3: Kaplan-Meier Curves for Overall Survival in Study 3

14.4 Pancreatic Cancer

The efficacy of gemcitabine was evaluated in two trials (Studies 5 and 6), a randomized, single-blind, two-arm, active-controlled trial (Study 5) conducted in patients with locally advanced or metastatic pancreatic cancer who had received no prior chemotherapy and in a single-arm, open-label, multicenter trial (Study 6) conducted in patients with locally advanced or metastatic pancreatic cancer previously treated with fluorouracil or a fluorouracil-containing regimen. In Study 5, patients were randomized to receive either gemcitabine 1000 mg/m^2 intravenously over 30 minutes once weekly for 7 weeks followed by a one-week rest, then once weekly for 3 consecutive weeks every 28-days in subsequent cycles (n=63) or fluorouracil 600 mg/m^2 intravenously over 30 minutes once weekly (n=63). In Study 6, all patients received gemcitabine 1000 mg/m^2 intravenously over 30 minutes once weekly for 7 weeks followed by a one-week rest, then once weekly for 3 consecutive weeks every 28-days in subsequent cycles.

The major efficacy outcome measure in both trials was "clinical benefit response". A patient was considered to have had a clinical benefit response if either of the following occurred:

- The patient achieved a ≥50% reduction in pain intensity (Memorial Pain Assessment Card) or analgesic consumption, or a 20-point or greater improvement in performance status (Karnofsky Performance Status) for a period of at least 4 consecutive weeks, without showing any sustained worsening in any of the other parameters. Sustained worsening was defined as 4 consecutive weeks with either any increase in pain intensity or analgesic consumption or a 20-point decrease in performance status occurring during the first 12 weeks of therapy.

OR

- The patient was stable on all of the aforementioned parameters, and showed a marked, sustained weight gain (≥7% increase maintained for ≥4 weeks) not due to fluid accumulation.

Study 5 enrolled 126 patients. Demographics and baseline characteristics were similar between the arms (Table 22).

The efficacy results are shown in Table 23 and Figure 4. Patients treated with gemcitabine had statistically significant increases in clinical benefit response, survival, and time to disease progression compared to those randomized to receive fluorouracil. No confirmed objective tumor responses were observed in either treatment arm.

Table 22: Baseline Demographics and Clinical Characteristics for Study 5
 | Gemcitabine; (N=63) | Fluorouracil; (N=63)
Male | 54% | 54%
Median age, years | 62 | 61
Range | 37 to 79 | 36 to 77
Stage IV disease | 71% | 76%
Baseline KPSa ≤70 | 70% | 68%
aKarnofsky Performance Status.

Table 23: Efficacy Results in Study 5
Efficacy Parameter | Gemcitabine (N=63) | Fluorouracil (N=63)
Clinical Benefit Response | 22.2% | 4.8%
p-valuea | p=0.004
Overall Survival
Median (95% CI) in months | 5.7 (4.7, 6.9) | 4.2 (3.1, 5.1)
p-valuea | p=0.0009
Time to Disease Progression
Median (95% CI) in months | 2.1 (1.9, 3.4) | 0.9 (0.9, 1.1)
p-valuea | p=0.0013
a p-value for clinical benefit response calculated using the two-sided test for difference in binomial proportions. All other p-values are calculated using log rank test.

Figure 4: Kaplan-Meier Curves for Overall Survival in Study 5

15 REFERENCES

1. "OSHA Hazardous Drugs." OSHA. http://www.osha.gov/SLTC/hazardousdrugs/index.html

16 HOW SUPPLIED/STORAGE AND HANDLING

AVGEMSITM Injection, is a clear and colorless to light straw-colored solution available in sterile multiple-dose vials individually packaged in a carton as follows:

- 200 mg/5.26 mL (38 mg/mL), NDC 83831-122-01
- 1 g/26.3 mL (38 mg/mL), NDC 83831-123-01
- 2 g/52.6 mL (38 mg/mL), NDC 83831-124-01

Store unopened multiple-dose vials at 2° to 8°C (36° to 46°F). Do not freeze.

AVGEMSI is a hazardous drug. Follow applicable special handling and disposal procedures.1

17 PATIENT COUNSELING INFORMATION

Myelosuppression

Advise patients of the risks of myelosuppression. Instruct patients to immediately contact their healthcare provider should any signs or symptoms of infection, including fever, or if bleeding, or signs of anemia, occur [see Warnings and Precautions (5.2)].

Severe Cutaneous Adverse Reactions (SCARs)

Advise patients of the risks of SCARs, including Stevens-Johnson syndrome (SJS), toxic epidermal necrolysis (TEN), drug reaction with eosinophilia and systemic symptoms (DRESS), and acute generalized exanthematous pustulosis (AGEP). Instruct patients to immediately contact their healthcare provider should any signs or symptoms of severe skin rash or skin peeling, blistering and/or mouth sores occur [see Warnings and Precautions (5.3)]

Pulmonary Toxicity

Advise patients of the risks of pulmonary toxicity, including respiratory failure and death. Instruct patients to immediately contact their healthcare provider for development of shortness of breath, wheezing, or cough [see Warnings and Precautions (5.4)].

Hemolytic Uremic Syndrome and Renal Failure

Advise patients of the risks of hemolytic uremic syndrome and associated renal failure. Instruct patients to immediately contact their healthcare provider for changes in the color or volume of urine output or for increased bruising or bleeding [see Warnings and Precautions (5.5)].

Hepatic Toxicity

Advise patients of the risks of hepatic toxicity including liver failure and death. Instruct patients to immediately contact their healthcare provider for signs of jaundice or for pain/tenderness in the right upper abdominal quadrant [see Warnings and Precautions (5.6)].

Embryo-Fetal Toxicity

Advise females and males of reproductive potential that AVGEMSI can cause fetal harm. Advise females of reproductive potential to use effective contraception during treatment with AVGEMSI and for 6 months after the final dose. Advise male patients with female partners of reproductive potential to use effective contraception during treatment with AVGEMSI and for 3 months after the final dose [see Warnings and Precaution (5.7), Use in Specific Populations (8.1, 8.3)].

Lactation

Advise women not to breastfeed during treatment with AVGEMSI and for at least one week after the last dose [see Use in Specific Populations (8.2)].

Infertility

Advise males of reproductive potential of the potential for reduced fertility with AVGEMSI [see Use in Specific Populations (8.3), Nonclinical Toxicology (13.1)].

Rx Only

Manufactured for:

Avyxa Pharma, LLC

New Jersey 07054, USA

Made in Switzerland

1204-0001

Revised: 07/2025

PRINCIPAL DISPLAY PANEL

NDC 83831-123-01

AVGEMSITM
(gemcitabine) Injection

1 g/26.3 mL

(38 mg/mL)

For Intravenous Infusion After Dilution

WARNING: Hazardous Drug

One Multiple-Dose Vial

Rx Only

Label

Carton

NDC 83831-124-01

AVGEMSITM
(gemcitabine) Injection

2 g/52.6 mL

(38 mg/mL)

For Intravenous Infusion After Dilution

WARNING: Hazardous Drug

One Multiple-Dose Vial

Rx Only

Label

Carton